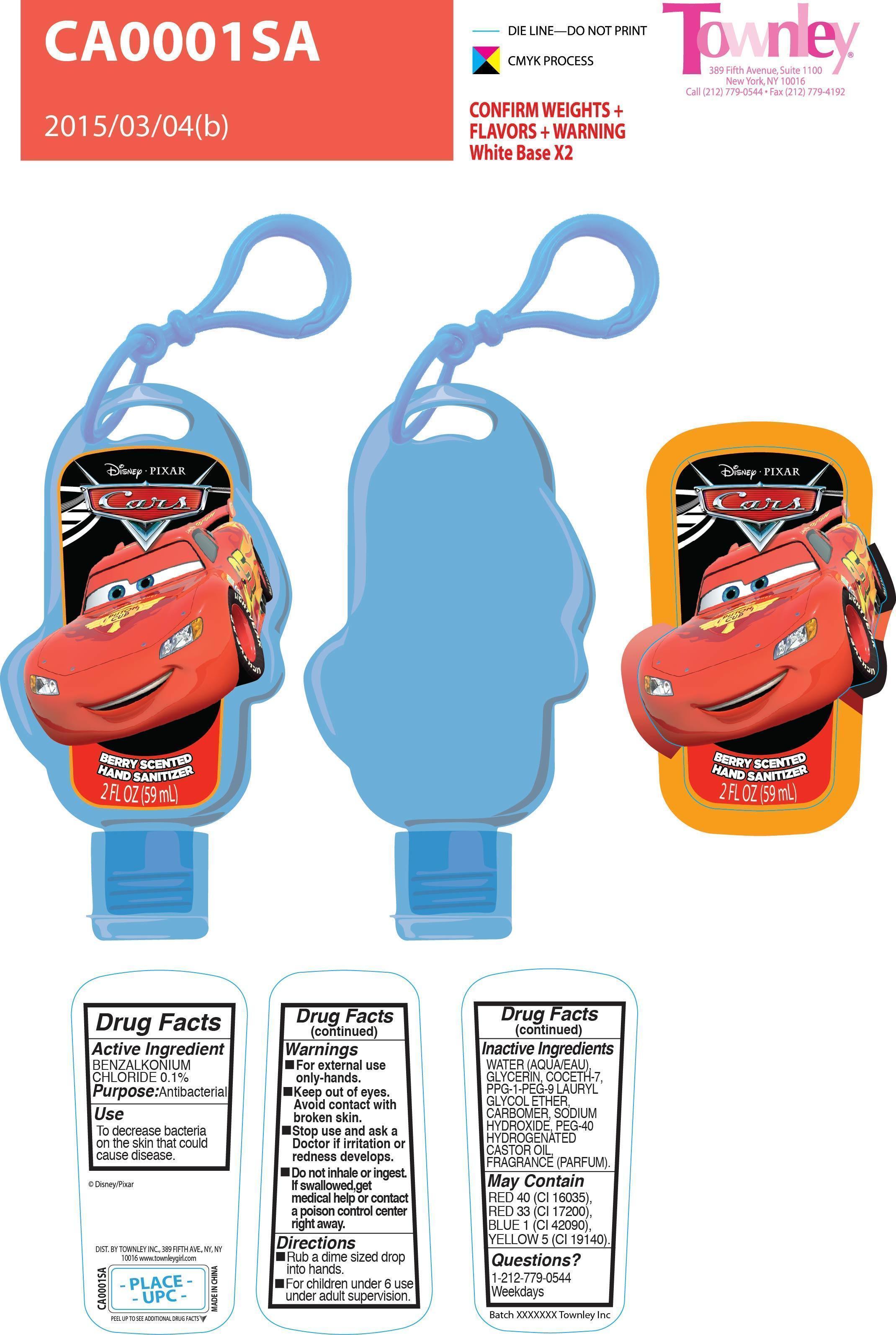 DRUG LABEL: Berry Scented Hand Sanitizer
NDC: 69157-001 | Form: GEL
Manufacturer: Foshan Nanhai Jinxiong Toys C o., Ltd
Category: otc | Type: HUMAN OTC DRUG LABEL
Date: 20150403

ACTIVE INGREDIENTS: BENZALKONIUM CHLORIDE 0.06 mg/59 mg
INACTIVE INGREDIENTS: WATER; GLYCERIN; COCETH-7 CARBOXYLIC ACID; PPG-1 TRIDECETH-6; CARBOMER HOMOPOLYMER TYPE C (ALLYL PENTAERYTHRITOL CROSSLINKED); SODIUM HYDROXIDE; PEG-40 CASTOR OIL; FD&C RED NO. 40; D&C RED NO. 33; FD&C BLUE NO. 1; FD&C YELLOW NO. 5

Active Ingredient

Benzalkonium Chloride 0.1%

Purpose

Antibacterial

Use

To decrease bacteria on the skin that could cause disease.

keep out of reach of children

INDICATIONS AND USAGE

May Contain

Red 40 (Cl 16035)

Red 33 (Cl 17200)

Blue 1 (Cl42045)

Yellow 5 (Cl 19140)

Warnings

- For external use only-hands.
- Keep out of eyes. Avoid contact with broken skin.
- Stop use and ask a Doctor if irritation or redness develops.
- Do not inhale or ingest. If swallowed, get medical help or contact a poison control center right away.

Directions

- Rub a dime sized drop into hands.
- For children under 6 use under adult supervision.

Inactive Ingredients

water (aqua/eau), glycerin, coceth-7, ppg-1-peg-9 lauryl glycol etyher, carbomer, sodium hydroxide, peg-40 hydrogenated castor oil, fragrance/parfum.